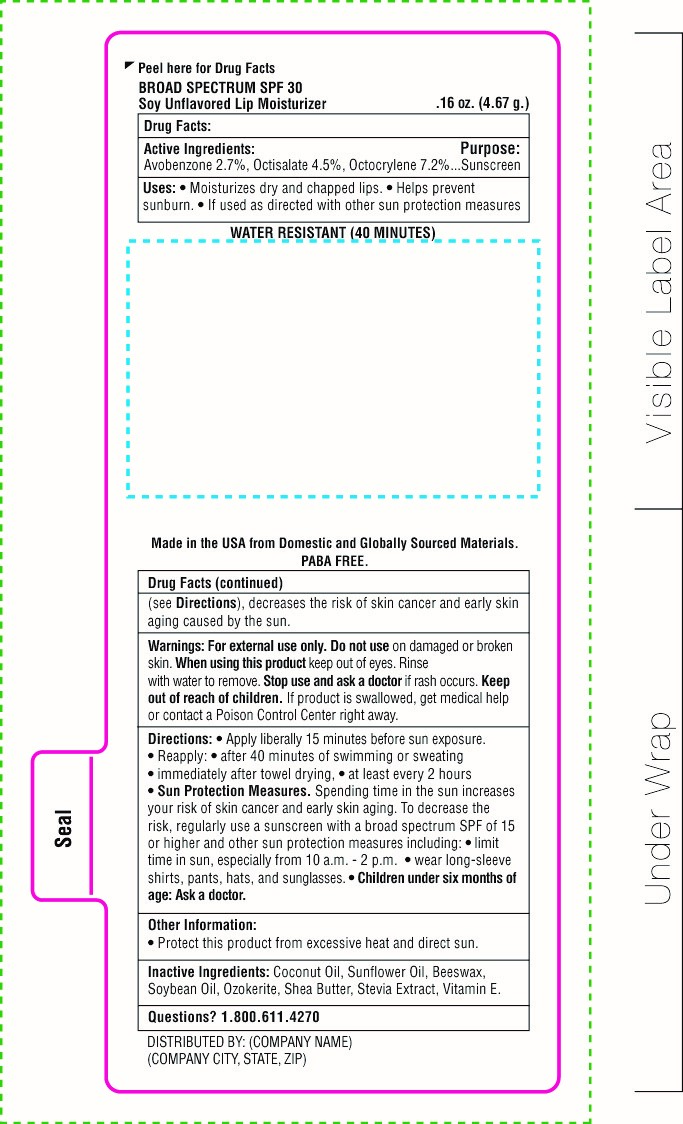 DRUG LABEL: SnugZ SPF 30 Soy Lip Balm
NDC: 76309-100 | Form: STICK
Manufacturer: SnugZ/USA, LLC
Category: otc | Type: HUMAN OTC DRUG LABEL
Date: 20251229

ACTIVE INGREDIENTS: OCTISALATE 0.23 g/4.67 g; OCTOCRYLENE 0.37 g/4.67 g; AVOBENZONE 0.14 g/4.67 g
INACTIVE INGREDIENTS: WHITE WAX

ZLBS - SPF 30 Soy Lip Balm